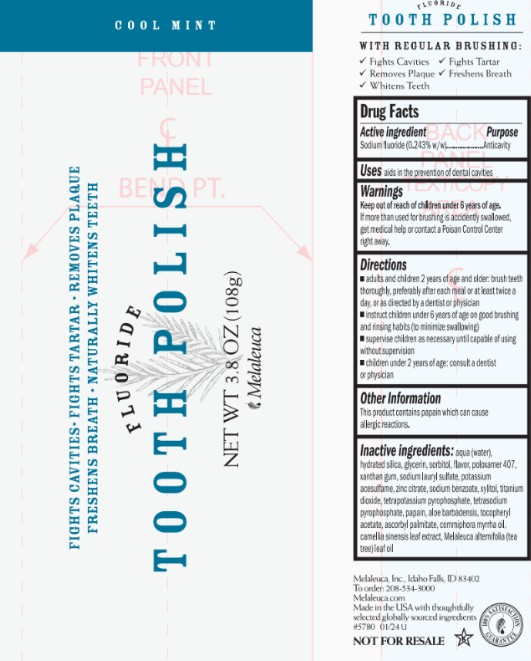 DRUG LABEL: Whitening
NDC: 54473-301 | Form: PASTE
Manufacturer: Melaleuca, Inc.
Category: otc | Type: HUMAN OTC DRUG LABEL
Date: 20251231

ACTIVE INGREDIENTS: SODIUM FLUORIDE 0.26244 g/108 g
INACTIVE INGREDIENTS: ALOE VERA LEAF; ASCORBYL PALMITATE; GREEN TEA LEAF; MYRRH OIL; GLYCERIN; HYDRATED SILICA; TEA TREE OIL; PAPAIN; POLOXAMER 407; ACESULFAME POTASSIUM; SODIUM LAURYL SULFATE; SODIUM BENZOATE; SORBITOL; POTASSIUM PYROPHOSPHATE; SODIUM PYROPHOSPHATE; TITANIUM DIOXIDE; ALPHA-TOCOPHEROL ACETATE; WATER; XANTHAN GUM; XYLITOL

Classic Tooth Polish Cool Mint with Fluoride

Active ingredient
Sodium Fluoride (0.243%)

Purpose
Anticavity

INDICATIONS AND USAGE

Use aids in the prevention of dental cavities

Warnings

Keep out of reach of children under 6 years of age. If more than used for brushing is accidentally swallowed, get medical help or contact a Poison Control Center right away. Warning: This product contains propolis, which can cause allergic reactions.

Directions

- adults and children 2 years of age and older: brush teeth thoroughly, preferably after each meal or at least twice a day, or as directed by a dentist or physician
- instruct children under 6 years of age on good brushing and rinsing habits (to minimize swallowing)
- supervise children as necessary until capable of using without supervision
- children under 2 years of age: consult a dentist or physician

INACTIVE INGREDIENT

Inactive ingredients: aloe barbadensis, ascorbyl palmitate, camellia sinensis leaf extract, commiphora myrrha oil, flavor, glycerin, hydrated silica, melaleuca alternifolia (tea tree) leaf oil, papain, poloxamer 407, potassium acesulfame, propolis extract, sodium alkyl sulfate, sodium benzoate, sorbitol, tetrapotassium pyrophosphate, tetrasodium pyrophosphate, titanium dioxide, tocopheryl acetate, water, xanthan gum, xylitol